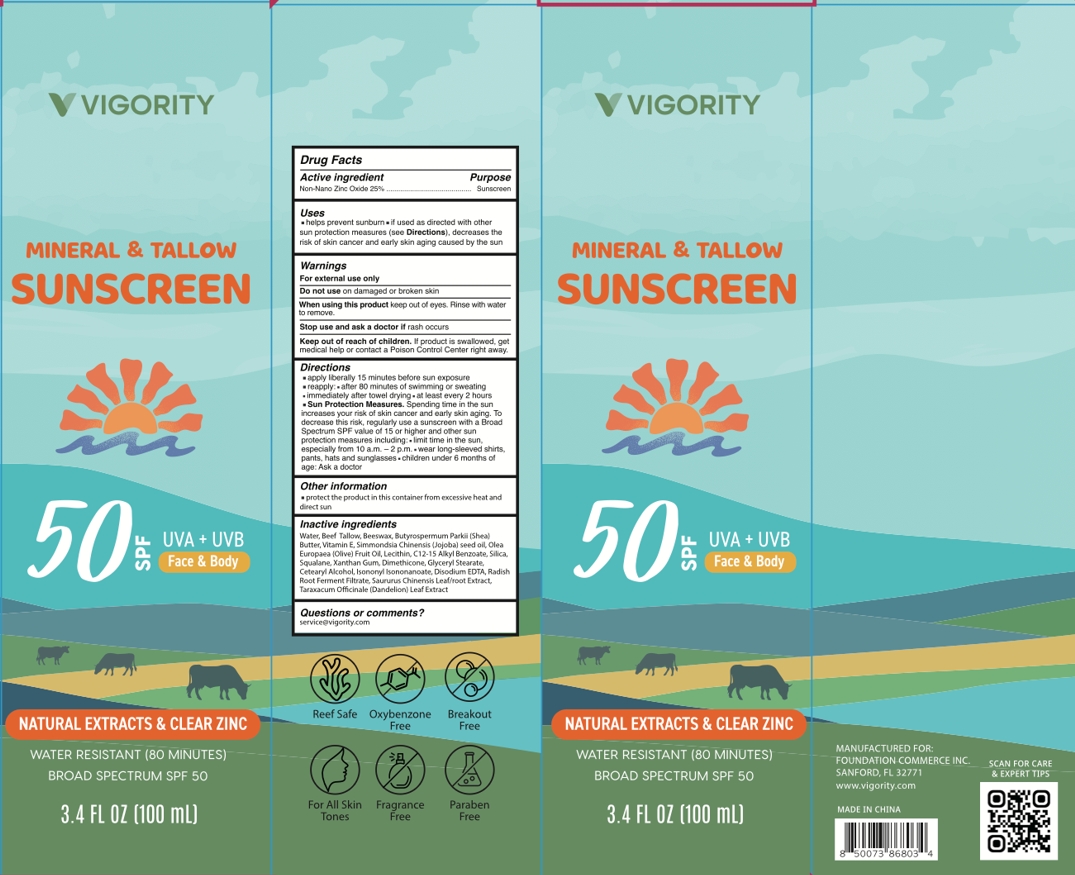 DRUG LABEL: TALLOW SUNSCREEN
NDC: 85739-001 | Form: CREAM
Manufacturer: FOUNDATION COMMERCE INC
Category: otc | Type: HUMAN OTC DRUG LABEL
Date: 20250528

ACTIVE INGREDIENTS: ZINC OXIDE 25 mg/100 mL
INACTIVE INGREDIENTS: TARAXACUM OFFICINALE (DANDELION) ROOT; SILICON DIOXIDE; XANTHAN GUM; DIMETHICONE 1000; LECITHIN, SOYBEAN; ISONONYL ISONONANOATE; WATER; OLEA EUROPAEA (OLIVE) FRUIT OIL; C12-15 ALKYL BENZOATE; CETEARYL ALCOHOL; CALCIUM DISODIUM EDTA; SQUALANE; SAURURUS CHINENSIS WHOLE; BEEF TALLOW; BEESWAX; BUTYROSPERMUM PARKII (SHEA) BUTTER; VITAMIN E POLYETHYLENE GLYCOL SUCCINATE; SIMMONDSIA CHINENSIS (JOJOBA) SEED OIL; LEUCONOSTOC/RADISH ROOT FERMENT FILTRATE; GLYCERYL STEARATE

Initial Drug Listing - TALLOW SUNSCREEN

ACTIVE INGREDIENT

Non-Nano Zinc Oxide 25%

PURPOSE

Sunscreen

INDICATIONS AND USAGE

- Helps prevent sunburn
- If used as directed with othersun protection measures (see Directions), decreases the risk of skin cancer and early skin aging caused by the sun

WARNINGS

For external use only

DO NOT USE

on damaged or broken skin

WHEN USING

Keep out of eyes. Rinse with water to remowe.

Ask a doctor if rash occurs.

KEEP OUT OF REACH OF CHILDREN

lf product is swallowed, get medical help or contact a Poison Control Center right away.

DOSAGE AND ADMINISTRATION

- Apply liberally 15 minutes belore sun exposure.
- Reapply: after 80 minutes of swimming or sweating.immediately after towel drying at least every 2 hours.
- Sun Protection Measures. Spending time in the sunincreases your risk of skin cancer and eariy skin aging. Todecrease this risk, regularly use a sunscreen wiih a BroadSpectrum SPF value ot 15 or higher and other sunprotection measures including:
  - limit time in the sun,especially from 10 a.m.-2 p.m.
  - wear long-sleeved shirts,pants, hats and sunglasses
  - children under 6 months ofage: Ask a doclor

OTHER SAFETY INFORMATION

Protect the product in this container from excessive heat and direct sun

INACTIVE INGREDIENT

Water, Beef Tallow, Beeswax, Butyrospermum Parkii {Shea)Butter, Vitamin E, Simmondsia Chinensis (Jojoba) seed oll, OleaEuropaea (Olive) Fruit Oil, Lecithin,C12-15 Alkyl Benzoate, Silica,Squalane, Xanthan Gum, Dimethicone, Glyceryl Stearate,Cetearyl Alcohol, lsononyi lsononanoate, Disodium EDTA, RadishRoot Ferment Filtrate, Saururus Chinensis Leaf/root Extract,Taraxacum Offcinale (Dandelion) Leaf Extract

QUESTIONS

servicegvigority.com